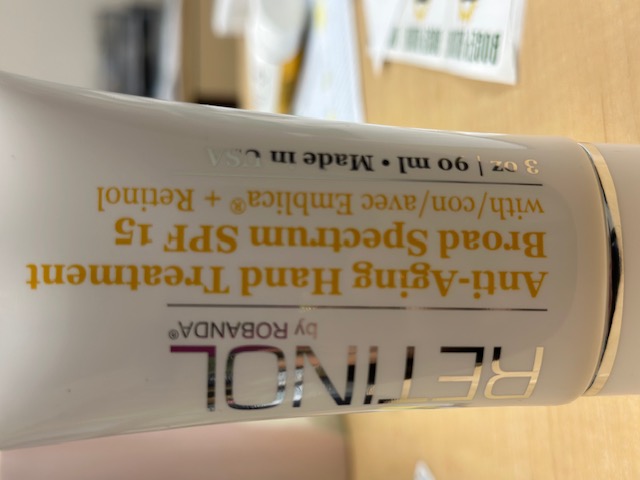 DRUG LABEL: Robanda Anti-Aging Hand
NDC: 53950-7007 | Form: LOTION
Manufacturer: Robanda International, Inc.
Category: otc | Type: HUMAN OTC DRUG LABEL
Date: 20251103

ACTIVE INGREDIENTS: AVOBENZONE 1 mg/100 mL; OCTINOXATE 7.5 mg/100 mL; OCTISALATE 5 mg/100 mL; OXYBENZONE 6 mg/100 mL
INACTIVE INGREDIENTS: GLYCERIN; ALKYL (C12-15) BENZOATE; STEARIC ACID; GLYCERYL MONOSTEARATE; CETYL ALCOHOL; DIMETHYL CAPRAMIDE; PEG-100 STEARATE; TROLAMINE; PHYLLANTHUS EMBLICA FRUIT; LECITHIN, SOYBEAN; CARBOMER COPOLYMER TYPE B (ALLYL PENTAERYTHRITOL CROSSLINKED); VITAMIN A ACETATE; RETINOL; EDETATE SODIUM; .ALPHA.-TOCOPHEROL ACETATE; TOCOPHEROL; SQUALANE; SHEANUT OIL; PHENOXYETHANOL; HYDROXYETHYL ACRYLATE/SODIUM ACRYLOYLDIMETHYL TAURATE COPOLYMER (45000 MPA.S AT 1%); ETHYLHEXYLGLYCERIN; POLYSORBATE 60; TITANIUM DIOXIDE; FD&C YELLOW NO. 5; FD&C RED NO. 40; DIMETHICONE; WATER

RO20-Robanda International Anti-Aging Hand Treatment (53950-7007)

Active ingredient

Avobenzone (1%)

Octinoxate (7.5%)

Octisilate (5%)

Oxybenzone (6%)

Purpose

Sunscreen

Keep Out of Reach of Children

If product is swallowed, get medical help or contact a Poison Control Center right away.

Uses

- Helps treat and prevent aging of the hands
- Reduces freckle spots, wrinkles, & fine lines
- Skin lightener with anti-aging and antioxidant properties

Warnings

For external use only.

When using this product

- Keep out of eyes. Rinse with water to remove.

Stop use and ask doctor if

- Rash or irritation develops and lasts.

Directions

Apply to hands twice daily, or as desired.

Inactive ingredients

Water, Dimethicone, Glycerin, C12-15 Alkyl Benzoate, Stearic Acid, Glyceryl Stearate, Cetyl Alcohol, Dimethyl Capramide, PEG-100 Stearate, Triethanolamine, Phyllanthus Embilica (Fruit) Extract, Hydroxylated Soy Lethicin, Carbomer, Retinyl Acetate, Retinol, Tetrasodium EDTA, Tocopherol Acetate, Tocopherol, Squalane, Butyrospermum Parkii (Shea Butter), Phenoxyethanol, Hydroxyethyl Acrylate/Sodium Acryloyl Dimethyltaurate Copolymer, Ethylhexylglycerin, Polysorbate 60, Titanium Dioxide, Yellow 5 (CI 19140), Red 40 (CI 16035)

Robanda International, Inc.

San Diego, CA, 92110, U.S.A.

Edgware, Middx, HA8 9TA, U.K.

P:(800) 783.9969

P:(619) 276.7660

F:(619) 276.7661

www. robanda.com